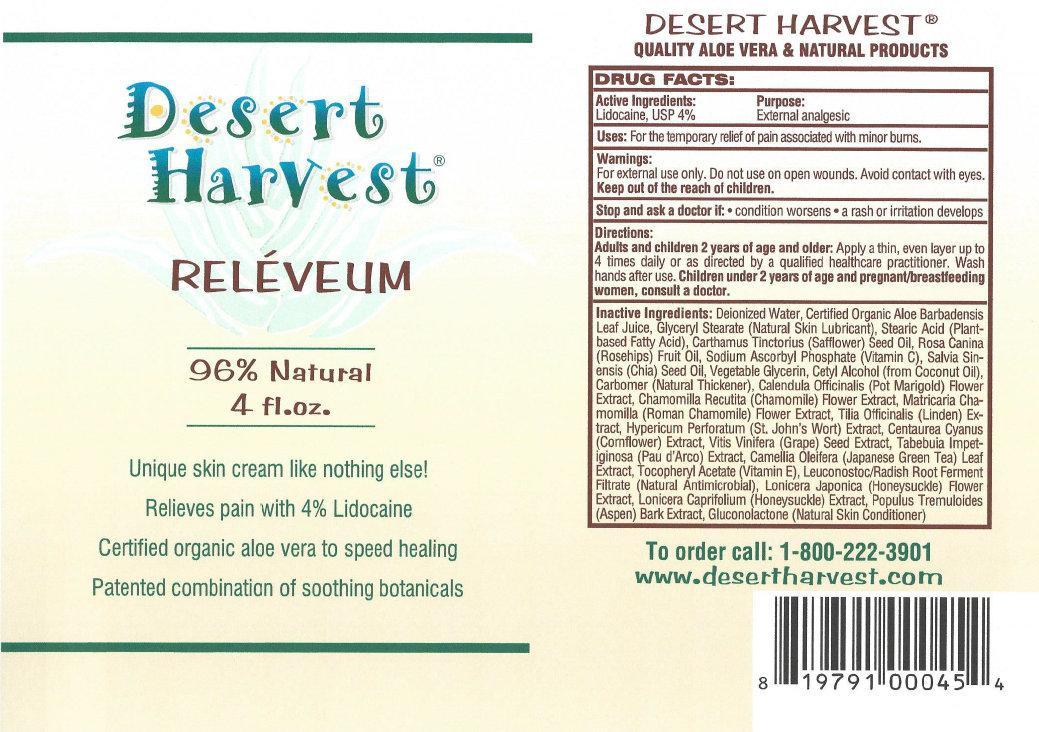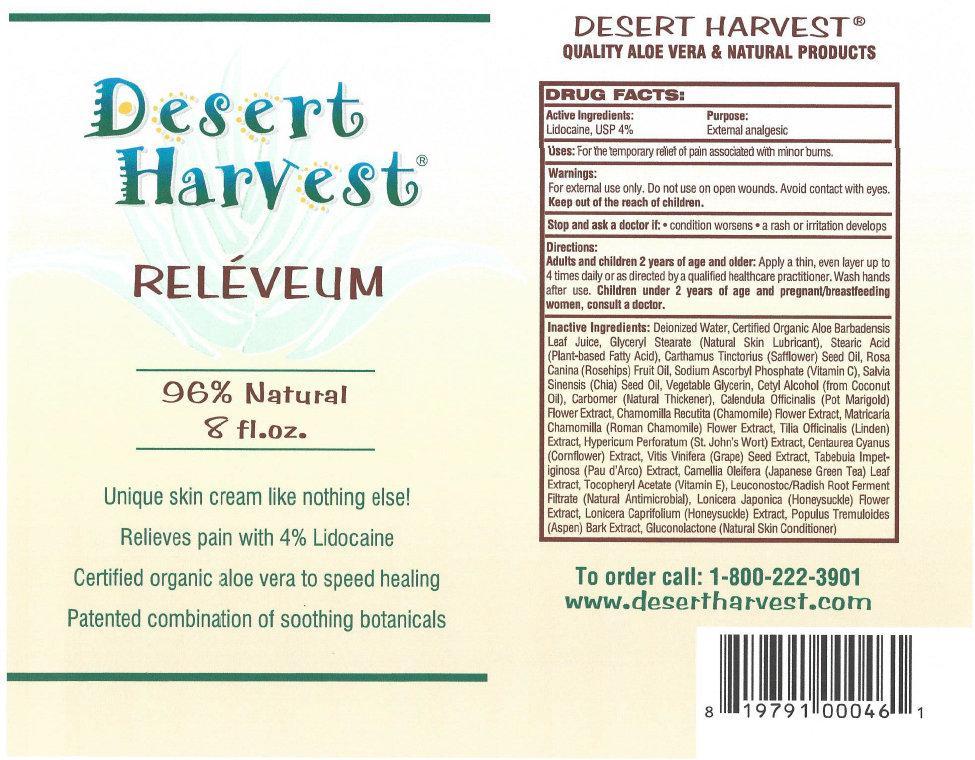 DRUG LABEL: Desert Harvest RELEVEUM
NDC: 69145-201 | Form: CREAM
Manufacturer: Desert Harvest Inc.
Category: otc | Type: HUMAN OTC DRUG LABEL
Date: 20231105

ACTIVE INGREDIENTS: LIDOCAINE 40 mg/1 mL
INACTIVE INGREDIENTS: WATER; ALOE VERA LEAF; GLYCERYL MONOSTEARATE; STEARIC ACID; SAFFLOWER OIL; ROSA CANINA FRUIT OIL; SODIUM ASCORBYL PHOSPHATE; CHIA SEED OIL; GLYCERIN; CETYL ALCOHOL; CALENDULA OFFICINALIS FLOWER; CHAMOMILE; CHAMAEMELUM NOBILE FLOWER; TILIA CORDATA FLOWER; ST. JOHN'S WORT; CENTAUREA CYANUS FLOWER; VITIS VINIFERA SEED; TABEBUIA IMPETIGINOSA WHOLE; CAMELLIA OLEIFERA LEAF; .ALPHA.-TOCOPHEROL; LEUCONOSTOC/RADISH ROOT FERMENT FILTRATE; LONICERA JAPONICA FLOWER; LONICERA CAPRIFOLIUM FLOWER; POPULUS TREMULOIDES BARK; GLUCONOLACTONE

Desert Harvest RELEVEUM

Active Ingredients:

Lidocaine, USP 4%

Purpose:

External analgesic

Uses:

For the temporary relief of pain associated with minor burns.

Warnings:

For external use only. Do not use on open wounds. Avoid contact with eyes.

Stop use and ask a doctor if:

- condition worsens
- a rash or irritation develops

Directions:

Apply a thin, even later up to 4 times daily or as directed by a qualified healthcare practitioner. Wash hands after use. Adults and children 2 years of age and older: Children under 2 years of age and pregnant/breastfeeding women, consult a doctor.

Inactive ingredients

Deionized Water, Certified Organic Aloe Barbadensis Leaf Juice, Glyceryl Stearate (Natural Skin Lubricant), Stearic Acid (Plant-based Fatty Acid), Cartharnus Tinctorius (Safflower) Seed Oil, Rosa Canina (Rosehips) Fruit Oil, Sodium Ascorbyl Phosphate (Vitamin C), Salvia Sin-ensis (Chia) Seed Oil, Vegetable Glycerin, Cetyl Alcohol (from Coconut Oil), Carbomer (Natural Thickener), Calendula Officitialis (Pot Marigold) Flower i Extract, Chamomilla Recutita (Chamomile) Flower Extract, Matrlcarla Cha-mornilla (Roman Chamomile) Flower Extract, Tilia Oficinalis (Linden) Ex-tract, Hypericum Perforatum (St. John's Wort) Extract, Centaurea Cyanus (Cornflower) Extract, Vitis Vinifera (Grape) Seed Extract, Tabebuia Impetiginosa (Pau d'Arco) Extract, Camellia Oleifera (Japanese Green Tea) Leaf Extract, Tocopheryl Acetate (Vitamin E), Leuconostoc/Radish Root Ferment Filtrate (Natural Antimicrobial), Lonicera Japonica (Honeysuckle) Flower Extract, Lonicera Caprifolium (Honeysuckle) Extract, Populus Tremuloides (Aspen) Bark Extract, Gluconolactone (Natural Skin Conditioner)